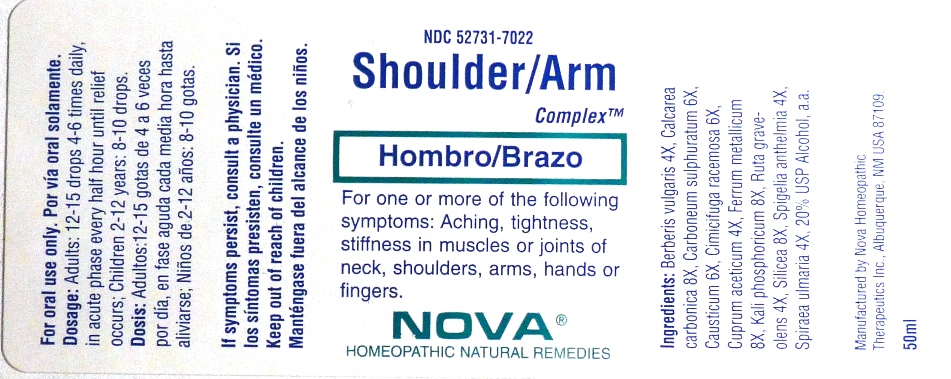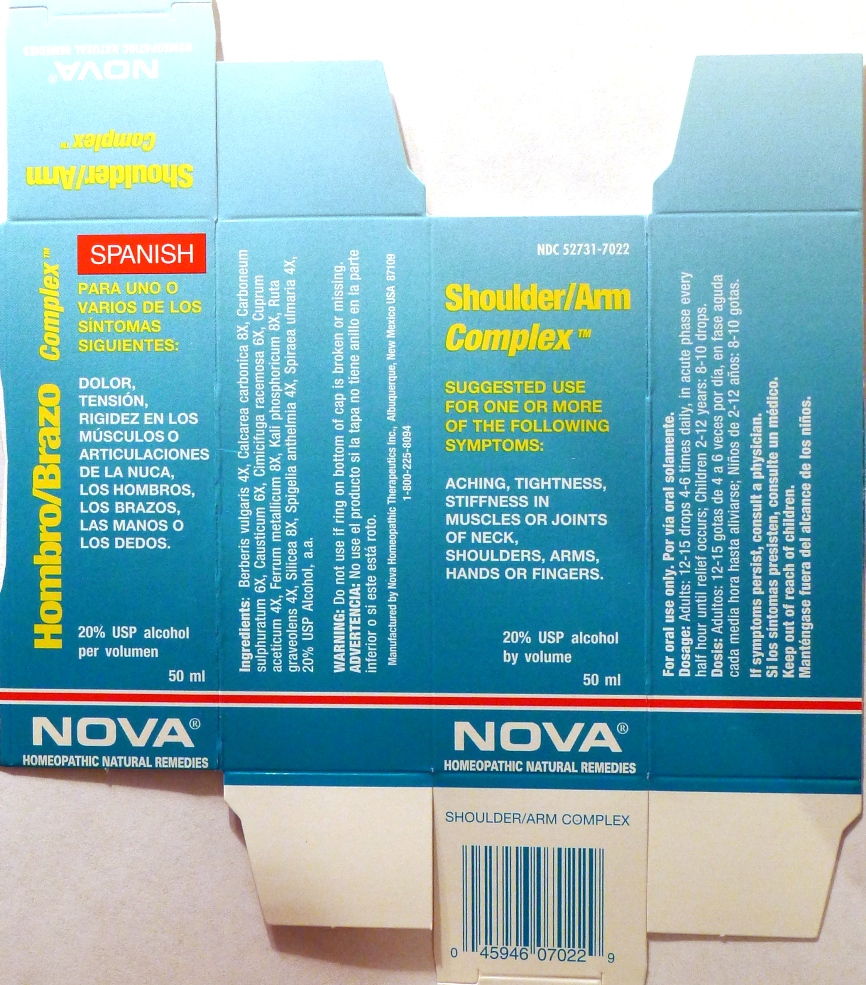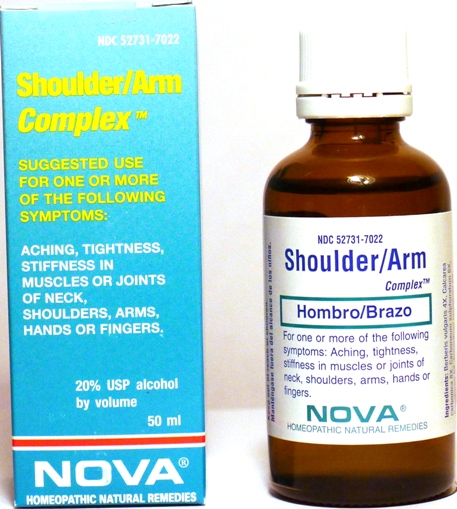 DRUG LABEL: Shoulder/Arm Complex
NDC: 52731-7022 | Form: LIQUID
Manufacturer: Nova Homeopathic Therapeutics, Inc.
Category: homeopathic | Type: HUMAN OTC DRUG LABEL
Date: 20110601

ACTIVE INGREDIENTS: BERBERIS VULGARIS ROOT BARK 4 [hp_X]/1 mL; OYSTER SHELL CALCIUM CARBONATE, CRUDE 8 [hp_X]/1 mL; CARBON DISULFIDE 6 [hp_X]/1 mL; CAUSTICUM 6 [hp_X]/1 mL; BLACK COHOSH 6 [hp_X]/1 mL; CUPRIC ACETATE 4 [hp_X]/1 mL; IRON 8 [hp_X]/1 mL; POTASSIUM PHOSPHATE, DIBASIC 8 [hp_X]/1 mL; RUTA GRAVEOLENS FLOWERING TOP 4 [hp_X]/1 mL; SILICON DIOXIDE 8 [hp_X]/1 mL; SPIGELIA ANTHELMIA 4 [hp_X]/1 mL; FILIPENDULA ULMARIA ROOT 4 [hp_X]/1 mL
INACTIVE INGREDIENTS: ALCOHOL

Shoulder/Arm Complex

Purpose:

Suggested use for one or more of the following symptoms:

Aching, tightness, stiffness in muscles or joints of neck, shoulders, arms, hands or fingers.

Usage and Dosage:

For oral use only.

DOSAGE AND ADMINISTRATION

Adults:
In Acute Phase:
12-15 drops, every half hour until relief occurs
When Relief Occurs:
12-15 drops, 4-6 times per day
Children 2-12 years:
8-10 drops, 4-6 times per day

Warnings:

Keep out of reach of children

WARNINGS

If symptoms persist, consult a physician.
Do not use if ring on bottom of cap is broken or missing.

Active Ingredients:

Berberis vulgaris 4X, Calcarea carbonica 8X, Carboneum sulphuratum 6X, Causticum 6X, Cimicifuga racemosa 6X, Cuprum aceticum 4X, Ferrum metallicum 8X, Kali phosphoricum 8X, Ruta graveolens 4X, Silicea 8X, Spigelia anthelmia 4X, Spiraea ulmaria 4X

Inactive Ingredients:

Alcohol, 20% USP

QUESTIONS

Manufactured by Nova Homeopathic Therapeutics Inc., Albuquerque, New Mexico USA 87109
1-800-225-8094

PACKAGE LABEL

Shoulder/Arm Complex Product

Shoulder/Arm Complex Bottle Label

Shoulder/Arm Complex Box